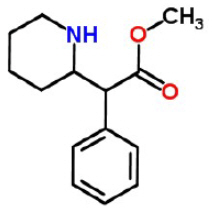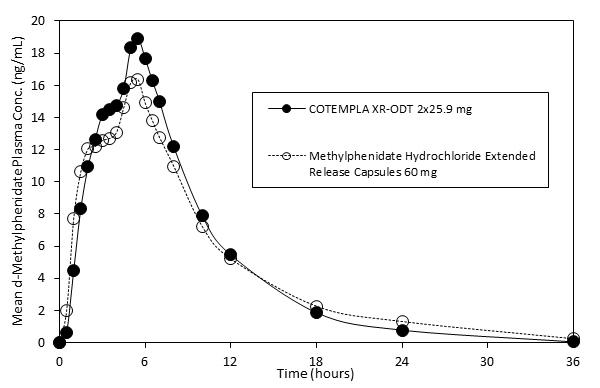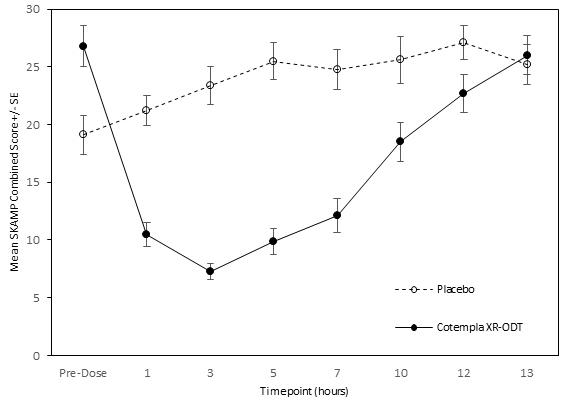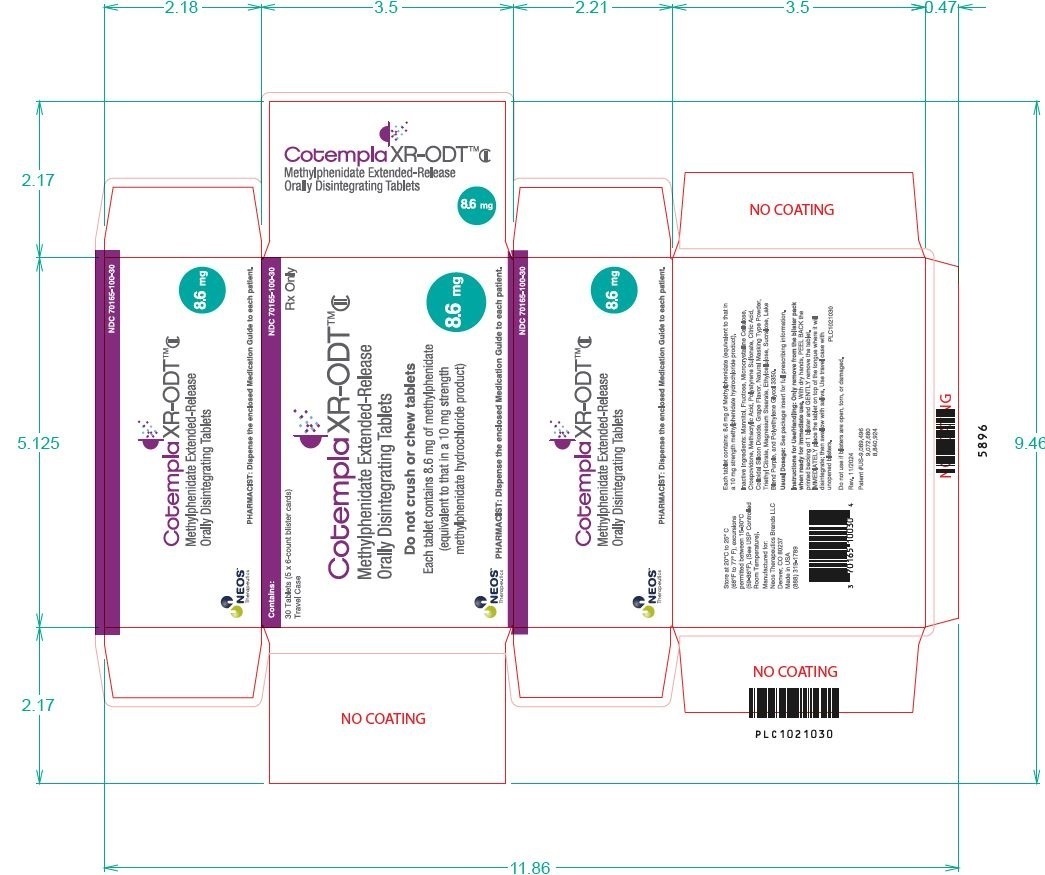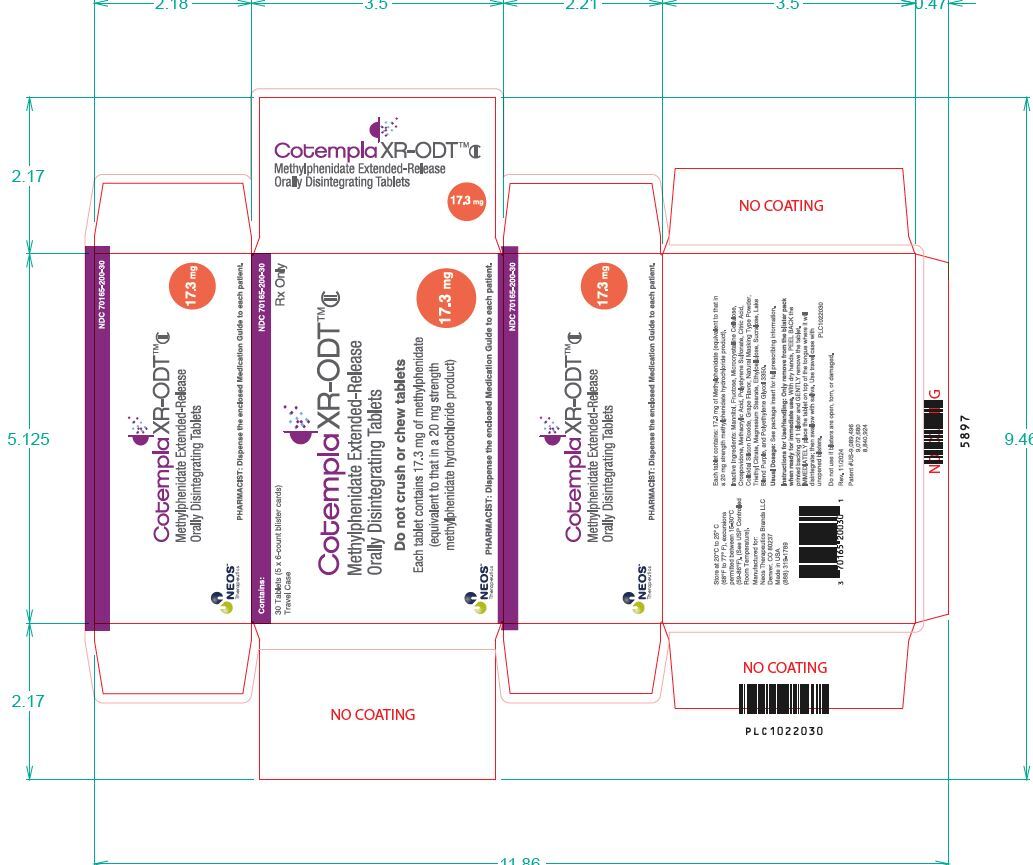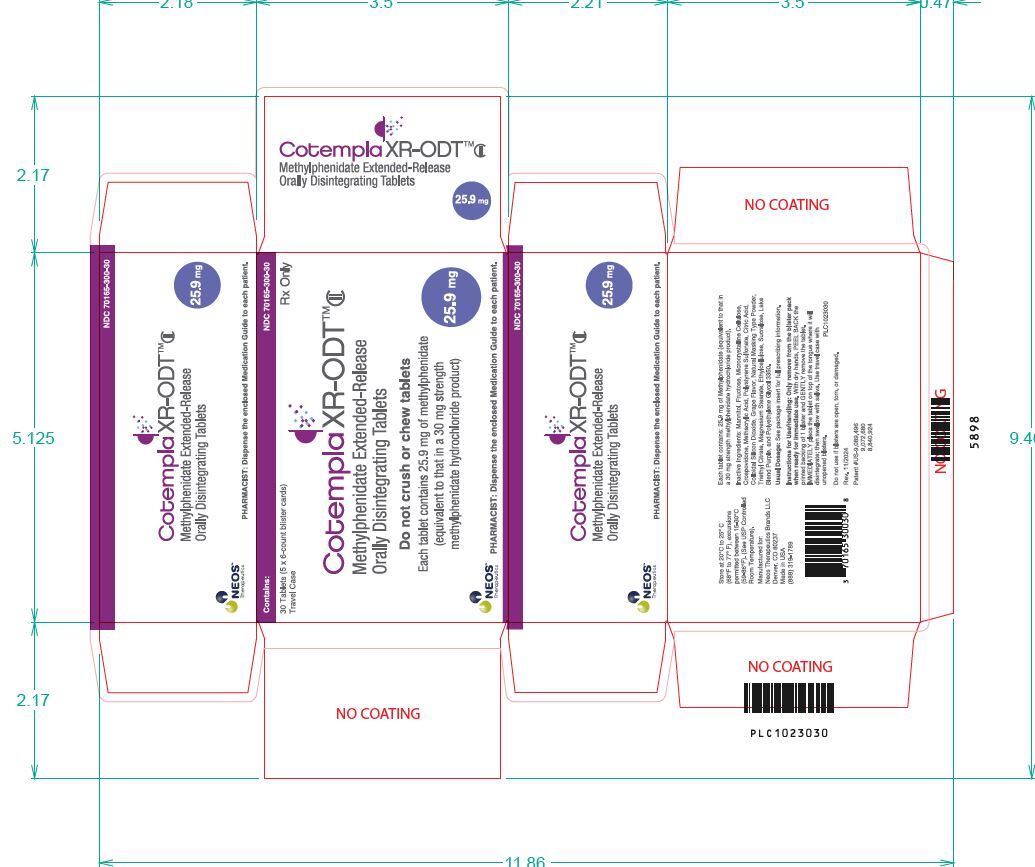 DRUG LABEL: Cotempla XR-ODT
NDC: 70165-100 | Form: TABLET, ORALLY DISINTEGRATING
Manufacturer: Neos Therapeutics Brands, LLC
Category: prescription | Type: HUMAN PRESCRIPTION DRUG LABEL
Date: 20250924
DEA Schedule: CII

ACTIVE INGREDIENTS: METHYLPHENIDATE 8.6 mg/1 1
INACTIVE INGREDIENTS: METHACRYLIC ACID; POLYSTYRENE SULFONIC ACID; CITRIC ACID MONOHYDRATE; SILICON DIOXIDE; TRIETHYL CITRATE; MAGNESIUM STEARATE; ETHYLCELLULOSE, UNSPECIFIED; SUCRALOSE; POLYETHYLENE GLYCOL, UNSPECIFIED; MANNITOL; FRUCTOSE; MICROCRYSTALLINE CELLULOSE; CROSPOVIDONE

HIGHLIGHTS OF PRESCRIBING INFORMATION

These highlights do not include all the information needed to use COTEMPLA XR-ODT safely and effectively. See full prescribing information for COTEMPLA XR-ODT.
COTEMPLA XR-ODT (methylphenidate extended-release orally disintegrating tablets), CII
Initial U.S. Approval: 1955

WARNING: ABUSE, MISUSE, AND ADDICTION

See full prescribing information for complete boxed warning.

COTEMPLA XR-ODT has a high potential for abuse and misuse, which can lead to the development of a substance use disorder, including addiction. Misuse and abuse of CNS stimulants, including COTEMPLA XR-ODT, can result in overdose and death (5.1, 9.2, 10):

• Before prescribing COTEMPLA XR-ODT, assess each patient’s risk for abuse, misuse, and addiction.

• Educate patients and their families about these risks, proper storage of the drug, and proper disposal of any unused drug.

• Throughout treatment, reassess each patient’s risk and frequently monitor for signs and symptoms of abuse, misuse, and addiction.

1 INDICATIONS AND USAGE

COTEMPLA XR-ODT is a central nervous system (CNS) stimulant indicated for the treatment of Attention Deficit Hyperactivity Disorder (ADHD) in pediatric patients 6 to 17 years of age. (1)

Limitations of Use

The use of COTEMPLA XR-ODT is not recommended in pediatric patients younger than 6 years of age because they had higher plasma exposure and a higher incidence of adverse reactions (e.g., weight loss) than patients 6 years and older at the same dosage. (5.7, 8.4)

3 DOSAGE FORMS AND STRENGTHS

Extended-release orally disintegrating tablets: 8.6 mg, 17.3 mg, 25.9 mg. (3)

2 DOSAGE AND ADMINISTRATION

- Recommended starting dose for pediatric patients 6 to 17 years of age is 17.3 mg given orally once daily in the morning. Dosage may be increased weekly in increments of 8.6 mg to 17.3 mg per day. Daily dosage above 51.8 mg is not recommended. (2.2)
- Patients are advised to take COTEMPLA XR-ODT consistently either with food or without food. (2.2)

4 CONTRAINDICATIONS

- Known hypersensitivity to methylphenidate or product components. (4)
- Concurrent treatment with a monoamine oxidase inhibitor (MAOI), or use of an MAOI within the preceding 14 days. (4)

5 WARNINGS AND PRECAUTIONS

- Risks to Patients with Serious Cardiac Disease: Avoid use in patients with known structural cardiac abnormalities, cardiomyopathy, serious cardiac arrhythmias, coronary artery disease, or other serious cardiac disease. (5.2)
- Increased Blood Pressure and Heart Rate: Monitor blood pressure and pulse. Consider the benefits and risks in patients for whom an increase in blood pressure or heart rate would be problematic. (5.3)
- Psychiatric Adverse Reactions: Prior to initiating COTEMPLA XR-ODT, screen patients for risk factors for developing a manic episode. If new psychotic or manic symptoms occur, consider discontinuing COTEMPLA XR-ODT. (5.4)
- Priapism: If abnormally sustained or frequent and painful erection occur, patients should seek immediate medical attention. (5.5)
- Peripheral Vasculopathy, including Raynaud's Phenomenon: Careful observation for digital changes is necessary during COTEMPLA XR-ODT treatment. Further clinical evaluation (e.g., rheumatology referral) may be appropriate for patients who develop signs or symptoms of perifphral vasculophathy. (5.6)
- Long-term Suppression of Growth in Pediactric Patients: Closely monitor growth (height and weight) in pediatric patients. Pediatric patients not growing or gaining height or weight as expected may need to have their treatment interrupted. (5.7)
- Acute Angle Closure Glaucoma: COTEMPLA XR-ODT-treated patients considered at risk for acute angle closure glaucoma (e.g., patients with significant hyperopia) should be evaluated by an ophthalmologist. (5.8)
- Increased Intraocular Pressure (IOP) and Glaucoma: Prescribe COTEMPLA XR-ODT to patients with open-angle glaucoma or abnormally increased IOP only if the benefit of treatment is considered to outweigh the risk. Closely monitor patients with a history of increased IOP or open angle glaucoma. (5.9)
- Motor and Verbal Tics and Worsening of Tourette’s Syndrome: Before initiating COTEMPLA XR-ODT, assess the family history and clinically evaluate patients for tics or Tourette’s syndrome. Regularly monitor patients for the emergence or worsening of tics or Tourette’s syndrome. Discontinue treatment if clinically appropriate. (5.10)

6 ADVERSE REACTIONS

Based on accumulated data from other methylphenidate products, the most common (>5% and twice the rate of placebo) adverse reactions are appetite decreased, insomnia, nausea, vomiting, dyspepsia, abdominal pain, weight decreased, anxiety, dizziness, irritability, affect lability, tachycardia, and blood pressure increased. (6)

To report SUSPECTED ADVERSE REACTIONS, contact Neos Therapeutics, Inc. at 1-888-319-1789 or http://www.COTEMPLAXRODT.com or FDA at 1-800-FDA-1088 or www.fda.gov/medwatch.

7 DRUG INTERACTIONS

- Antihypertensive Drugs: Monitor blood pressure. Adjust dosage of antihypertensive drug as needed. (7)

RECENT MAJOR CHANGES

Indications and Usage (1) 09/2025
Warnings and Precautions (5.7) 09/2025

FULL PRESCRIBING INFORMATION

WARNING: ABUSE, MISUSE, AND ADDICTION

COTEMPLA XR-ODT has a high potential for abuse and misuse, which can lead to the development of a substance use disorder, including addiction. Misuse and abuse of CNS stimulants, including COTEMPLA XR-ODT, can result in overdose and death (5.1, 9.2, 10). Before prescribing COTEMPLA XR-ODT, assess each patient’s risk for abuse, misuse, and addiction. Educate patients and their families about these risks, proper storage of the drug, and proper disposal of any unused drug. Throughout treatment, reassess each patient’s risk and frequently monitor for signs and symptoms of abuse, misuse, and addiction.

1 INDICATIONS AND USAGE

COTEMPLA XR-ODT is indicated for the treatment of Attention Deficit Hyperactivity Disorder (ADHD) in pediatric patients 6 to 17 years of age [see Clinical Studies (14)].

Limitations of Use

The use of COTEMPLA XR-ODT is not recommended in pediatric patients younger than 6 years of age because they had higher plasma exposure and a higher incidence of adverse reactions (e.g., weight loss) than patients 6 years and older at the same dosage [see Warnings and Precautions (5.7). Use in Specific Populations (8.4)].

3 DOSAGE FORMS AND STRENGTHS

- 8.6 mg extended-release orally disintegrating tablet: round, purple to light purple mottled (debossed "T1" on one side and plain on the other)
- 17.3 mg extended-release orally disintegrating tablet: round, purple to light purple mottled (debossed "T2" on one side and plain on the other)
- 25.9 mg extended-release orally disintegrating tablet: round, purple to light purple mottled (debossed "T3" on one side and plain on the other)

2 DOSAGE AND ADMINISTRATION

2.1 Pretreatment Screening

Prior to treating patients with COTEMPLA XR-ODT, assess:

- for the presence of cardiac disease (i.e. perform a careful history, family history of sudden death or ventricular arrhythmia, and physical exam) [see Warnings and Precautions (5.2)] .
- the family history and clinically evaluate patients for motor or verbal tics or Tourette's sydrome before initiating COTEMPLA XR-ODT [see Warnings and Precautions (5.10)].

2.2 General Dosing Information

COTEMPLA XR-ODT is given orally once daily in the morning.

Advise patients to take COTEMPLA XR-ODT consistently either with food or without food [see Clinical Pharmacology (12.3)] .

The recommended starting dose of COTEMPLA XR-ODT for patients 6 to 17 years of age is 17.3 mg once daily in the morning. The dose may be titrated weekly in increments of 8.6 mg to 17.3 mg. Daily doses above 51.8 mg have not been studied and are not recommended.

The dose should be individualized according to the needs and responses of the patient.

2.3 Dosage Reduction and Discontinuation

If paradoxical aggravation of symptoms or other adverse reactions occur, reduce dosage, or, if necessary, discontinue COTEMPLA XR-ODT. If improvement is not observed after appropriate dosage adjustment over a one-month period, discontinue COTEMPLA XR-ODT.

2.4 COTEMPLA XR-ODT Administration

Instruct the patient or caregiver on the following administration instructions:

- Do not remove the tablet from the blister pack until just prior to dosing. Take the tablet immediately after opening the blister pack. Do not store the tablet for future use.
- Use dry hands when opening the blister pack.
- Remove the tablet by peeling back the foil on the blister pack. Do not push the tablet through the foil.
- As soon as the blister is opened, remove the tablet and place on the patient's tongue.
- Place the whole tablet on the tongue and allow it to disintegrate without chewing or crushing.
- The tablet will disintegrate in saliva so that it can be swallowed. No liquid is needed to take the tablet.

4 CONTRAINDICATIONS

COTEMPLA XR-ODT is contraindicated in patients with:

- Known hypersensitivity to methylphenidate or other components of COTEMPLA XR-ODT. Hypersensitivity reactions such as angioedema and anaphylactic reactions have been reported in patients treated with methylphenidate products [see Adverse Reactions (6.2)] .
- Concomitant treatment with monoamine oxidase inhibitors (MAOIs), and also within a minimum of 14 days following discontinuation of treatment with a monoamine oxidase inhibitor because of the risk of hypertensive crisis [see Drug Interactions (7.1)] .

5 WARNINGS AND PRECAUTIONS

.

5.1 Abuse, Misuse, and Addiction

COTEMPLA XR-ODT has a high potential for abuse and misuse. The use of COTEMPLA XR-ODT exposes individuals to the risks of abuse and misuse, which can lead to the development of a substance use disorder, including addiction. COTEMPLA XR-ODT can be diverted for nonmedical use into illicit channels or distribution [see Drug Abuse and Dependence (9.2)]. Misuse and abuse of CNS stimulants, including COTEMPLA XR-ODT, can result in overdose and death [see Overdosage (10)], and this risk is increased with higher doses or unapproved methods of administration, such as snorting or injection.

Before prescribing COTEMPLA XR-ODT, assess each patient’s risk for abuse, misuse, and addiction. Educate patients and their families about these risks and proper disposal of any unused drug. Advise patients to store COTEMPLA XR-ODT in a safe place, preferably locked, and instruct patients to not give COTEMPLA XR-ODT to anyone else. Throughout COTEMPLA XR-ODT treatment, reassess each patient’s risk of abuse, misuse, and addiction and frequently monitor for signs and symptoms of abuse, misuse, and addiction.

5.2 Risks to Patients with Serious Cardiac Disease

Sudden death has occurred in patients with structural cardiac abnormalities or other serious cardiac disease who were treated with CNS stimulants at the recommended ADHD dosages. Avoid COTEMPLA XR-ODT use in patients with known structural cardiac abnormalities, cardiomyopathy, serious cardiac arrhythmia, coronary artery disease, or other serious cardiac disease.

5.3 Increased Blood Pressure and Heart Rate

CNS stimulants cause an increase in blood pressure (mean increase approximately 2 to 4 mm Hg) and heart rate (mean increase approximately 3 to 6 bpm). Some patients may have larger increases.
Monitor all COTEMPLA XR-ODT-treated patients for hypertension and tachycardia.

5.5 Priapism

Prolonged and painful erections, sometimes requiring surgical intervention, have been reported with methylphenidate use in both adult and pediatric male patients. Although priapism was not reported with methylphenidate initiation, it developed after some time on methylphenidate, often subsequent to an increase in dosage. Priapism also occurred during methylphenidate withdrawal (drug holidays or during discontinuation).

COTEMPLA XR-ODT-treated patients who develop abnormally sustained or frequent and painful erections should seek immediate medical attention.

5.4 Psychiatric Adverse Reactions

Exacerbation of Pre-Existing Psychosis

CNS stimulants may exacerbate symptoms of behavior disturbance and thought disorder in patients with a pre-existing psychotic disorder.

Induction of a Manic Episode in Patients with Bipolar Disorder

CNS stimulants may induce a manic or mixed episode in patients. Prior to initiating COTEMPLA XR-ODT treatment, screen patients for risk factors for developing a manic episode (e.g. comorbid or history of depressive symptoms or a family history of suicide, bipolar disorder, or depression).

New Psychotic or Manic Symptoms

CNS stimulants, at the recommended dosage, may cause psychotic or manic symptoms (e.g., hallucinations, delusional thinking or mania) in patients without a prior history of psychotic illness or mania. In a pooled analysis of multiple short-term, placebo-controlled studies of CNS stimulants, psychotic or manic symptoms occurred in approximately 0.1% of CNS stimulant-treated patients, compared to 0% of placebo-treated patients. If such symptoms occur, consider discontinuing COTEMPLA XR-ODT.

5.6 Peripheral Vasculopathy, including Raynaud's Phenomenon

CNS stimulants, including COTEMPLA XR-ODT, used to treat ADHD are associated with peripheral vasculopathy, including Raynaud’s phenomenon. Signs and symptoms are usually intermittent and mild; however, sequelae have included digital ulceration and/or soft tissue breakdown. Effects of peripheral vasculopathy, including Raynaud’s phenomenon, were observed in post-marketing reports and at the therapeutic dosages of CNS stimulants in all age groups throughout the course of treatment. Signs and symptoms generally improved after dosage reduction or discontinuation of the CNS stimulant.

Careful observation for digital changes is necessary during COTEMPLA XR-ODT treatment. Further clinical evaluation (e.g., rheumatology referral) may be appropriate for COTEMPLA XRODT-treated patients who develop signs or symptoms of peripheral vasculopathy.

5.7 Long-Term Suppression of Growth in Pediatric Patients

COTEMPLA[A1] XR-ODT is not approved for use and is not recommended in pediatric patients below 6 years of age [see Use in Specific Populations (8.4)].

CNS stimulants have been associated with weight loss and slowing of growth rate in pediatric patients.

Careful follow-up of weight and height in pediatric patients ages 7 to 10 years who were randomized to either methylphenidate or nonmedication-treatment groups over 14 months, as well as in naturalistic subgroups of newly methylphenidate-treated and nonmedication-treated pediatric patients over 36 months (to the ages of 10 to 13 years), suggests that pediatric patients who received methylphenidate for 7 days per week throughout the year had a temporary slowing in growth rate (on average, a total of about 2 cm less growth in height and 2.7 kg less growth in weight over 3 years), without evidence of growth rebound during this development period.

Closely monitor growth (weight and height) in COTEMPLA XR-ODT-treated pediatric patients. Pediatric patients who are not growing or gaining height or weight as expected may need to have their treatment interrupted.

5.8 Acute Angle Closure Glaucoma

There have been reports of angle closure glaucoma associated with methylphenidate treatment.

Although the mechanism is not clear, COTEMPLA XR-ODT-treated patients considered at risk for acute angle closure glaucoma (e.g., patients with significant hyperopia) should be evaluated by an ophthalmologist.

5.9 Increased Intraocular Pressure and Glaucoma

There have been reports of an elevation of intraocular pressure (IOP) associated with methylphenidate treatment [see Adverse Reactions (6.2)].

Prescribe COTEMPLA XR-ODT to patients with open-angle glaucoma or abnormally increased IOP only if the benefit of treatment is considered to outweigh the risk. Closely monitor COTEMPLA XR-ODT-treated patients with a history of abnormally increased IOP or open angle glaucoma.

5.10 Motor and Verbal Tics, and Worsening of Tourette's Syndrome

CNS stimulants, including methylphenidate, have been associated with the onset or exacerbation of motor and verbal tics. Worsening of Tourette's syndrome has also been reported [see Adverse Reactions (6.2)].

Before initiating COTEMPLA XR-ODT, assess the family history and clinically evaluate patients for tics or Tourette's syndrome. Regulary monitor COTEMPLA XR-ODT-treated patients for the emergence or worsening of tics or Tourette's syndrome, and discontine treatment if clinically appropriate.

6 ADVERSE REACTIONS

The following are discussed in more detail in other sections of the labeling:

- Known hypersensitivity to methylphenidate or other ingredients of Cotempla XR-ODT [see Contraindications (4)]
- Hypertensive crisis when used concomitantly with monoamine oxidase inhibitors [see Contraindications (4) and Drug Interactions (7.1)]
- Abuse, Misuse, and Addiction [see Boxed Warning, Warnings and Precautions (5.1), and Drug Abuse and Dependence (9.2, 9.3)]
- Risks to patients with serious cardiac disease [see Warnings and Precautions (5.2)]
- Increased blood pressure and heart rate [see Warnings and Precautions (5.3)]
- Psychiatric adverse reactions [see Warnings and Precautions (5.4)]
- Priapism [see Warnings and Precautions (5.5)]
- Peripheral vasculopathy, including Raynaud's phenomenon [see Warnings and Precautions (5.6)]
- Long-term suppression of growth in pediatric patients [see Warnings and Precautions (5.7)]
- Acute Angle Closure Glaucoma [see Warnings and Precautions (5.8)]
- Increased Intraocular Pressure and Glaucoma [see Warnings and Precautions (5.9)]
- Motor and Verbal Tics, and Worsening of Tourette’s Syndrome [ see Warnings and Precautions (5.10)]

6.1 Clinical Trials Experience

Because clinical trials are conducted under widely varying conditions, adverse reaction rates observed in the clinical trials of a drug cannot be directly compared to rates in the clinical trials of another drug and may not reflect the rates observed in clinical practice.

Adverse Reactions in Studies with Other Methylphenidate Products in Children, Adolescents, and Adults with ADHD

Commonly reported (≥2% of the methylphenidate group and at least twice the rate of the placebo group) adverse reactions from placebo-controlled trials of methylphenidate products include: appetite decreased, weight decreased, nausea, abdominal pain, dyspepsia, dry mouth, vomiting, insomnia, anxiety, nervousness, restlessness, affect lability, agitation, irritability, dizziness, vertigo, tremor, blurred vision, blood pressure increased, heart rate increased, tachycardia, palpitations, hyperhidrosis, and pyrexia.

Adverse Reactions in Studies with COTEMPLA XR-ODT in Children with ADHD

There is limited experience with COTEMPLA XR-ODT in controlled trials. Based on this limited experience, the adverse reaction profile of COTEMPLA XR-ODT appears similar to other methylphenidate extended release-products.

6.2 Postmarketing Experience

The following adverse reactions have been identified during post approval use of methylphenidate products. Because these reactions are reported voluntarily from a population of uncertain size, it is not possible to reliably estimate their frequency or establish a causal relationship to drug exposure. These adverse reactions are as follows:

Blood and Lymphatic System Disorders: Pancytopenia, Thrombocytopenia, Thrombocytopenic purpura

Cardiac Disorders: Angina pectoris, Bradycardia, Extrasystole, Supraventricular tachycardia, Ventricular extrasystole

Eye Disorders: Diplopia, Increased intraocolar pressure, Mydriasis, Visual impairment

General Disorders: Chest pain, Chest discomfort, Hyperpyrexia

Immune System Disorders: Hypersensitivity reactions such as Angioedema, Anaphylactic reactions, Auricular swelling, Bullous conditions, Exfoliative conditions, Urticarias, Pruritis NEC, Rashes, Eruptions, and Exanthemas NEC

Investigations: Alkaline phosphatase increased, Bilirubin increased, Hepatic enzyme increased, Platelet count decreased, White blood cell count abnormal

Musculoskeletal, Connective Tissue and Bone Disorders: Arthralgia, Myalgia, Muscle twitching, Rhabdomyolysis

Nervous System Disorders: Convulsion, Grand mal convulsion, Dyskinesia, Serotonin syndrome in combination with serotonergic drugs, Motor and Verbal Tics

Psychiatric Disorders: Disorientation, Hallucination, Hallucination auditory, Hallucination visual, Libido changes, Mania

Urogenital System: Priapism

Skin and Subcutaneous Tissue Disorders: Alopecia, Erythema

Vascular Disorders: Raynaud's phenomenon

7 DRUG INTERACTIONS

7.1 Clinically Important Interactions with COTEMPLA XR-ODT

Table 1: Drugs Having Clinically Important Interactions with Methylphenidate
Monoamine Oxidase Inhibitors (MAOI)
Clinical Impact: | Concomitant use of MAOIs and CNS stimulants can cause hypertensive crisis. Potential outcomes include death, stroke, myocardial infarction, aortic dissection, ophthalmological complications, eclampsia, pulmonary edema, and renal failure [see Contraindications (4)] .
Intervention: | Do not administer COTEMPLA-XR ODT concomitantly with MAOIs or within 14 days after discontinuing MAOI treatment.
Gastric pH Modulators
Clinical Impact: | May change the release profile and alter the pharmacodynamics of COTEMPLA-XR ODT.
Intervention: | Concomitant use of Cotempla XR-ODT with a gastric pH modulator (i.e., a H2-blocker or a proton pump inhibitor) is not recommended.
Antihypertensive Drugs
Clinical Impact: | Cotempla XR-ODT may decrease the effectiveness of drug used to treat hypertension [see Warnings and Precautions (5.3)].
Intervention: | Monitor blood pressure and adjust the dosage of the antihypertensive drug as needed.
Halogenated Anesthetics
Clinical Impact: | Concomitant use of halogenated anesthetics and COTEMPLA XR-ODT may increase the risk of sudden blood pressure and heart rate increase during surgery.
Intervention: | Avoid use of COTEMPLA XR-ODT in patients being treated with anesthetics on the day of surgery.
Risperidone
Clinical Impact: | Combined use of methylphenidate with risperidone when there is a change, whether an increase or decrease, in dosage of either or both medications, may increase the risk of extrapyramidal symptoms (EPS).
Intervention: | Monitor for signs of EPS.

8 USE IN SPECIFIC POPULATIONS

.

8.1 Pregnancy

Pregnancy Exposure Registry

There is a pregnancy exposure registry that monitors pregnancy outcomes in women exposed to COTEMPLA XR-ODT during pregnancy. Healthcare providers are encouraged to register patients by calling the National Pregnancy Registry for Psychostimulants at 1-866-961-2388.

Risk Summary

Published studies and postmarketing reports on methylphenidate use during pregnancy are insufficient to inform a drug-associated risk of adverse pregnancy-related outcomes [see Data] . There are risks to the fetus associated with the use of central nervous system (CNS) stimulants during pregnancy [see Clinical Considerations]. No teratogenic effects were observed in embryo-fetal development studies with oral administration of methylphenidate to pregnant rats and rabbits during organogenesis at doses 4 and 18 times, respectively, the maximum recommended human dose (MRHD) of 51.8 mg (as base). However, spina bifida was observed in rabbits at a dose 60 times the MRHD [see Data].

The estimated background risk of major birth defects and miscarriage for the indicated population is unknown. All pregnancies have a background risk of birth defect, loss, or other adverse outcomes. In the U.S. general population, the estimated background risk of major birth defects and miscarriage in clinically recognized pregnancies is 2-4% and 15-20%, respectively.

Clinical Considerations

Fetal/Neonatal adverse reactions

CNS stimulants, such as COTEMPLA XR-ODT, can cause vasoconstriction and thereby decrease placental perfusion. No fetal and/or neonatal adverse reactions have been reported with the use of therapeutic doses of methylphenidate during pregnancy; however, premature delivery and low birth weight infants have been reported in amphetamine-dependent mothers.

Data

Human Data

A limited number of pregnancies have been reported in published observational studies and postmarketing reports describing methylphenidate use during pregnancy. Due to the small number of methylphenidate-exposed pregnancies with known outcomes, these data cannot definitely establish or exclude any drug-associated risk during pregnancy. Methodological limitations of these observational studies include small sample size, concomitant use of other medications, lack of detail regarding dose and duration of exposure to methylphenidate and non-generalizability of the enrolled populations.

Animal Data

In studies conducted in rats and rabbits, methylphenidate was administered orally at doses of up to 75 and 200 mg/kg/day, respectively, during the period of organogenesis. Teratogenic effects (increased incidence of fetal spina bifida) were observed in rabbits at the highest dose, which is approximately 60 times the maximum recommended human dose (MRHD) of 51.8 mg (as base) for adolescents on a mg/m^2 basis. The no effect level for embryo-fetal development in rabbits was 60 mg/kg/day (18 times the MRHD for adolescent on a mg/m^2 basis). There was no evidence of specific teratogenic activity in rats, although increased incidences of fetal skeletal variations were seen at the highest dose level (11 times the MRHD on a mg/m^2 basis for adolescent), which was also maternally toxic. The no effect level for embryo-fetal development in rats was 25 mg/kg/day (4 times the MRHD on a mg/m^2 basis for adolescent).

8.2 Lactation

Risk Summary

Limited published literature, based on breast milk sampling from five mothers, reports that methylphenidate is present in human milk, which resulted in infant doses of 0.16% to 0.7% of the maternal weight-adjusted dosage and a milk/plasma ratio ranging between 1.1 and 2.7. There are no reports of adverse effects on the breastfed infant and no effects on milk production. Long-term neurodevelopmental effects on infants from stimulant exposure are unknown. The developmental and health benefits of breastfeeding should be considered along with the mother's clinical need for COTEMPLA XR-ODT and any potential adverse effects on the breastfed child from COTEMPLA XR-ODT or from the underlying maternal condition.

Clinical Considerations

Monitor breastfeeding infants for adverse reactions, such as agitation, insomnia, anorexia, and reduced weight gain.

8.4 Pediatric Use

The safety and effectiveness of COTEMPLA XR-ODT have not been established in pediatric patients below the age of 6 years.

In studies evaluating extended-release methylphenidate products, patients 4 to <6 years of age had higher systemic methylphenidate exposures than those observed in older pediatric patients at the same dosage. Pediatric patients 4 to <6 years of age also had a higher incidence of adverse reactions, including weight loss.

The safety and effectiveness of COTEMPLA XR-ODT have been established in pediatric patients 6 to 17 years of age in one adequate and well-controlled study in pediatric patients 6 to 12 years, pharmacokinetic data in adolescents, and safety information from other methyphenidate-containing products [see Clinical Pharmacology (12) and Clinical Studies (14)] .

Long Term Suppression Growth

Growth should be monitored during treatment with stimulants, including COTEMPLA XR-ODT. Children who are not growing or gaining weight as expected may need to have their treatment interrupted [see Warnings and Precautions (5.7)] .

Juvenile Animal Toxicity Data

Rats treated with methylphenidate early in the postnatal period through sexual maturation demonstrated a decrease in spontaneous locomotor activity in adulthood. A deficit in acquisition of a specific learning task was observed in females only. The doses at which these findings were observed are at least 6 times the maximum recommended human dose (MRHD) of 51.8 mg (as base) for pediatric patients on a mg/m^2 basis.

In the study conducted in young rats, methylphenidate was administered orally at doses of up to 100 mg/kg/day for 9 weeks, starting early in the postnatal period (postnatal day 7) and continuing through sexual maturity (postnatal week 10). When these animals were tested as adults (postnatal weeks 13-14), decreased spontaneous locomotor activity was observed in males and females previously treated with 50 mg/kg/day [approximately 6 times the MRHD of 51.8 mg (as base) on a mg/m^2 basis] or greater, and a deficit in the acquisition of a specific learning task was observed in females exposed to the highest dose (12 times the MRHD on a mg/m^2 basis). The no effect level for juvenile neurobehavioral development in rats was 5 mg/kg/day (half the MRHD on a mg/m^2 basis). The clinical significance of the long-term behavioral effects observed in rats is unknown.

8.5 Geriatric Use

COTEMPLA XR-ODT has not been studied in patients over the age of 65 years.

10 OVERDOSAGE

Clinical Effects of Overdose

Overdose of CNS stimulants is characterized by the following sympathomimetic effects:

- Cardiovascular effects including tachyarrhythmias, and hypertension or hypotension. Vasospasm, myocardial infarction, or aortic dissection may precipitate sudden cardiac death. Takotsubo cardiomyopathy may develop.
- CNS effects including psychomotor agitation, confusion, and hallucinations. Serotonin syndrome, seizures, cerebral vascular accidents, and coma may occur.
- Life-threatening hyperthermia (temperatures greater than 104⁰F) and rhabdomyolysis may develop.

Overdose Management

Consider the possibility of multiple drug ingestion. The pharmacokinetic profile of COTEMPLA XR-ODT should be considered when treating patients with overdose. Because methylphenidate has a large volume of distribution and is rapidly metabolized, dialysis is not useful. Consider contacting the Poison Help line (1-800-222-1222) or a medical toxicologist for additional overdose management recommendations.

9 DRUG ABUSE AND DEPENDENCE

9.1 Controlled Substance

COTEMPLA XR-ODT contains methylphenidate, a Schedule II controlled substance.

9.2 Abuse

COTEMPLA XR-ODT has a high potential for abuse and misuse which can lead to the development of a substance use disorder, including addiction [see Warnings and Precautions (5.1)]. COTEMPLA XR-ODT can be diverted for non-medical use into illicit channels or distribution.

Abuse is the intentional non-therapeutic use of a drug, even once, to achieve a desired psychological or physiological effect. Misuse is the intentional use, for therapeutic purposes, of a drug by an individual in a way other than prescribed by a health care provider or for whom it was not prescribed. Drug addiction is a cluster of behavioral, cognitive, and physiological phenomena that may include a strong desire to take the drug, difficulties in controlling drug use (e.g., continuing drug use despite harmful consequences, giving a higher priority to drug use than other activities and obligations), and possible tolerance or physical dependence.

Misuse and abuse of methylphenidate may cause increased heart rate, respiratory rate, or blood pressure; sweating; dilated pupils; hyperactivity; restlessness; insomnia; decreased appetite; loss of coordination; tremors; flushed skin; vomiting; and/or abdominal pain. Anxiety, psychosis, hostility, aggression, and suicidal or homicidal ideation have also been observed with CNS stimulants abuse and/or misuse. Misuse and abuse of CNS stimulants, including COTEMPLA XR-ODT, can result in overdose and death [see Overdosage (10)], and this risk is increased with higher doses or unapproved methods of administration, such as snorting or injection.

9.3 Dependence

Physical Dependence

COTEMPLA XR-ODT may produce physical dependence. Physical dependence is a state that develops as a result of physiological adaptation in response to repeated drug use, manifested by withdrawal signs and symptoms after abrupt discontinuation or a significant dose reduction of a drug.

Withdrawal signs and symptoms after abrupt discontinuation or dose reduction following prolonged use of CNS stimulants including COTEMPLA XR-ODT include dysphoric mood; depression; fatigue; vivid, unpleasant dreams; insomnia or hypersomnia; increased appetite; and psychomotor retardation or agitation.

Tolerance

COTEMPLA XR-ODT may produce tolerance. Tolerance is a physiological state characterized by a reduced response to a drug after repeated administration (i.e., a higher dose of a drug is required to produce the same effect that was once obtained at a lower dose).

11 DESCRIPTION

COTEMPLA XR-ODT contains methylphenidate, a central nervous system (CNS) stimulant. COTEMPLA XR-ODT is an extended-release orally disintegrating tablet intended for once daily administration. COTEMPLA XR-ODT contains approximately 25% immediate-release and 75% extended-release methylphenidate. Methylphenidate is ionically-bound to the sulfonate of polystyrene sulfonate particles.

COTEMPLA XR-ODT contains 8.6 mg, 17.3 mg or 25.9 mg of methylphenidate which is the same as the amount of methylphenidate (base equivalent) found, respectively, in 10 mg, 20 mg and 30 mg strength methylphenidate hydrochloride products.

The chemical name of methylphenidate is methyl α-phenyl-2-piperidineacetate, and its structural formula is shown in Figure 1.

Figure 1: Methylphenidate Structure

C14H19NO2 Mol. Wt. 233.31

COTEMPLA XR-ODT also contains the following inactive ingredients: Mannitol, Fructose, Microcrystalline Cellulose, Crospovidone, Methacrylic Acid, Polystyrene Sulfonate, Citric Acid, Colloidal Silicon Dioxide, Grape Flavor, Natural Masking Type Powder, Triethyl Citrate, Magnesium Stearate, Ethylcellulose, Sucralose, Lake Blend Purple, and Polyethylene Glycol 3350.

13 NONCLINICAL TOXICOLOGY

13.1 Carcinogenesis, Mutagenesis, Impairment of Fertility

Carcinogenesis

In a lifetime carcinogenicity study carried out in B6C3F1 mice, methylphenidate caused an increase in hepatocellular adenomas and, in males only, an increase in hepatoblastomas at a daily dose of approximately 60 mg/kg/day. For pediatric patients, this dose is approximately 4 times the maximum recommended human dose of 51.8 (as base) on a mg/m^2 basis. Hepatoblastoma is a relatively rare rodent malignant tumor type. There was no increase in total malignant hepatic tumors. The mouse strain used is sensitive to the development of hepatic tumors, and the significance of these results to humans is unknown.

Methylphenidate did not cause any increase in tumors in a lifetime carcinogenicity study carried out in F344 rats; the highest dose used was approximately 45 mg/kg/day, which is approximately 5 times the maximum recommended dose of 51.8 mg (as base) for pediatric patients on a mg/m^2 basis.

Mutagenesis

Methylphenidate was not mutagenic in the in vitro Ames reverse mutation assay or the in vitro mouse lymphoma cell forward mutation assay. Sister chromatid exchanges and chromosome aberrations were increased, indicative of a weak clastogenic response, in an in vitro assay in cultured Chinese Hamster Ovary (CHO) cells. Methylphenidate was negative in an in vivo mouse bone marrow micronucleus assay.

Impairment of Fertility

Methylphenidate did not impair fertility in male or female mice that were fed diets containing the drug in an 18-week Continuous Breeding study. The study was conducted at doses up to 160 mg/kg/day, approximately 12-fold the maximum recommended human dose of 51.8 (as base) for adolescents on a mg/m^2 basis.

12 CLINICAL PHARMACOLOGY

12.1 Mechanism of Action

Methylphenidate is a central nervous system (CNS) stimulant. The mode of therapeutic action in ADHD is not known.

12.2 Pharmacodynamics

Methylphenidate is a racemic mixture comprised of the d- and 1-isomers. The d-isomer is more pharmacologically active than the l-isomer. Methylphenidate is thought to block the reuptake of norepinephrine and dopamine into the presynaptic neuron and increase the release of these monoamines into the extraneuronal space.

12.3 Pharmacokinetics

After oral administration of COTEMPLA XR-ODT, circulation levels of l- methylphenidate (MPH) were about 2% of total MPH.

Elimination

Plasma methylphenidate concentrations decline monophasically following oral administration of COTEMPLA XR-ODT. The mean plasma terminal elimination half-life of methylphenidate was about 4 hours in healthy volunteers following a single 51.8 mg dose administration.

Metabolism

In humans, methylphenidate is metabolized primarily via deesterification to alpha-phenyl-piperidine acetic acid (ritalinic acid). The metabolite has little or no pharmacological activity.

Excretion

After oral dosing of radiolabeled methylphenidate in humans, about 90% of the radioactivity was recovered in urine. The main primary metabolite was PPAA, accounting for approximately 80% of the dose.

Absorption

Following a single dose of 51.8 mg (2×25.9 mg daily) COTEMPLA XR-ODT in healthy adult subjects under fasted conditions, plasma methylphenidate (MPH) reached maximal concentration (Cmax) at a median time of 5 hours after dosing. Compared to an extended release capsule formulation of methylphenidate, methylphenidate mean Cmax and exposure (AUCinf) was about 26% and 6% higher, respectively, after COTEMPLA XR-ODT administration (Figure 2).

Figure 2: Mean d-Methylphenidate Plasma Concentration-Time Profiles After Administration of COTEMPLA XR-ODT or Methylphenidate Hydrochloride Extended-Release Capsule in Healthy Volunteers Under Fasted Conditions

Effect of Food

Administration of 51.8 mg COTEMPLA XR-ODT with food (a high fat meal) decreased the Cmax and increased AUCinf of total MPH by approximately 24% and 16%, respectively. Food shortened the median time to peak concentration (Tmax) by 0.5 hour (fed: 4.5 hours vs. fasted: 5.0 hours).

Effect of Alcohol

There is no in vivo study conducted for the effect of alcohol on drug exposure. An in vitro dissolution study showed alcohol-induced dose dumping potential in the presence of 40% alcohol. Dose dumping was not observed in the presence of lower alcohol concentrations.

Specific Populations

Male and Female Patients and Ethnic Groups

There is insufficient experience with the use of COTEMPLA XR-ODT to detect gender or ethnic variations in pharmacokinetics.

Pediatric Patients

The pharmacokinetics of methylphenidate after COTEMPLA XR-ODT administration were studied in pediatric patients (6-17 years of age) with ADHD under fasted conditions. After a single oral dose of 51.8 mg COTEMPLA XR-ODT, plasma concentrations of methylphenidate in children (6-12 years of age) were approximately twice the concentrations observed in adults. Exposure levels in adolescent patients (13 -17 years of age) were similar to those in adults. Body weight normalized clearance values were similar across the age groups (Table 2).

Table 2: PK Parameters (Mean ±SD) of d-MPH After 51.8 mg Oral Dosing of COTEMPLA XR-ODT Under Fasted Conditions
PK Parameter | Children (n=24) | Adolescent (n=8) | Adult (n=38)
Tmax (hr)† | 4.6 (2.0-8.0) | 5.31 (3.5-8.0) | 4.98 (2.5 – 6.5)
T½ (hr) | 4.43±1.0 | 3.93±0.33 | 4.00±0.73
Cmax (ng/mL) | 32.7±9.83 | 20.2±5.79 | 20.8±5.22
Cl (L/hr/kg) | 6.21±1.48 | 5.54±1.19 | 5.48±1.46
AUC∞ (hr*ng/mL) | 328.9±90.21 | 187.2±62.05 | 169.1±57.13
† data presented as median range

Patients with Renal Impairment

There is no experience with the use of COTEMPLA XR-ODT in patients with renal insufficiency. After oral administration of radiolabeled methylphenidate in humans, methylphenidate was extensively metabolized and approximately 80% of the radioactivity was excreted in the urine in the form of PPAA. Since renal clearance is not an important route of methylphenidate clearance, renal insufficiency is expected to have little effect on the pharmacokinetics of COTEMPLA XR-ODT.

Patients with Hepatic Impairment

There is no experience with the use of COTEMPLA XR-ODT in patients with hepatic insufficiency.

Manufactured for Neos Therapeutics Brands, LLC. Denver, CO 80237. Made in USA.

For more information, call 1-888-319-1789

COTEMPLA XR-ODT is a registered trademark of Neos Therapeutics, Inc.

Copyright© 2014, Neos Therapeutics, Inc.

14 CLINICAL STUDIES

The efficacy of COTEMPLA XR-ODT was evaluated in a laboratory classroom study conducted in 87 pediatric patients (Aged 6 to 12 years) with ADHD. Following washout of previous methylphenidate medication, there was an open-label dose-optimization period (4 weeks) with an initial dose of 17.3 mg of COTEMPLA XR-ODT once daily in the morning. The dose could be titrated on a weekly basis from 17.3 mg, to 25.9 mg, to 34.6 mg, and up to 51.8 mg until an optimal dose or the maximum dose of 51.8 mg/day was reached. At the end of this period, subjects remained on their optimized dose for an additional week. Subjects then entered a 1-week randomized, double-blind, parallel group treatment period with the individually optimized dose of COTEMPLA XR-ODT or placebo. At the end of this week, raters evaluated the attention and behavior of the subjects in a laboratory classroom setting, using the Swanson, Kotkin, Agler, M-Flynn, and Pelham (SKAMP) rating scale SKAMP is a validated 13-item teacher-rated scale that assesses manifestations of ADHD in a classroom setting.

The primary efficacy endpoint was the average of the SKAMP-Combined (Attention and Deportment) scores over the test day (not including the baseline score), with assessments conducted at baseline, and 1, 3, 5, 7, 10, 12, and 13 hours post-dosing. The key secondary efficacy endpoints were onset and duration of effect, defined as the first point at which active drug separated from placebo on SKAMP-Combined scores and the last time point at which active drug separated from placebo on SKAMP-Combined scores, respectively.

The SKAMP-Combined scores test day average was statistically significantly lower (improved) with COTEMPLA XR-ODT compared to placebo (difference of -11 (95% CI: -13.9, -8.2)) (Table 3).

Table 3: Efficacy Analysis Results: SKAMP-Combined Scores Averaged Over Classroom Day in Patients with ADHD
Study Number | Treatment Group | Baseline Score at Randomizationa (SD) | Pre-dose Score on Classroom Dayb (SD) | LS Meanc (SE) | Placebo-subtracted Differenced (95% CI)
Study 1 | Cotempla XR-ODT (17.3-51.8 mg/day) | 21.1 (9.56) | 26.8 (11.52) | 14.3 (1.07) | -11.0 (-13.9, -8.2)
Study 1 | Placebo | 20.4 (9.09) | 19.1 (11.04) | 25.3 (1.16) | --
SD: standard deviation; SE: standard error; LS Mean: least-squares mean; CI: confidence interval.
a Visit 7 baseline score (Visit 7 occurred prior to the 1-week randomized, double-blind, parallel group treatment period).
b Visit 8 baseline score (Visit 8 occurred at the end of the 1-week randomized, double-blind, parallel group treatment period).
c Visit 8 LS mean over hours 1, 3, 5, 7, 10, 12, and 13.
d Difference (drug minus placebo) in least-squares means.

The SKAMP-Combined scores were also statistically significantly lower (improved) at time points (1, 3, 5, 7, 10, 12 hours) post-dosing with COTEMPLA XR-ODT compared to placebo (Figure 3).

Figure 3: LS Mean SKAMP Combined Score After Treatment with COTEMPLA XR-ODT or Placebo During Classroom Day in Patients with ADHD

*SE = Standard Error

The database was not large enough to assess whether there were differences in effects in age, gender, or race subgroups.

16 HOW SUPPLIED/STORAGE AND HANDLING

COTEMPLA XR-ODT Extended Release Orally Disintegrating Tablets are available in three strengths:

- 8.6 mg tablets, round, purple to light purple, mottled, and debossed "T1" on one side of the tablet;
- 17.3 mg tablets, round, purple to light purple, mottled, and debossed "T2" on one side of the tablet;
- 25.9 mg tablets, round, purple to light purple, mottled, and debossed "T3" on one side of the tablet.

They are available as follows:

NDC 70165-100-30 | 8.6 mg tablets: carton containing 5 blister cards of 6 tablets each, for a total of 30 tablets with a reusable travel case.
NDC 70165-200-30 | 17.3 mg tablets: carton containing 5 blister cards of 6 tablets each, for a total of 30 tablets with a reusable travel case.
NDC 70165-300-30 | 25.9 mg tablets: carton containing 5 blister cards of 6 tablets each, for a total of 30 tablets with a reusable travel case.

STORAGE AND HANDLING

Store at 20°C to 25°C (68°F to 77°F); excursions permitted from 15°C to 30°C (59°F to 86°F) [see USP Controlled Room Temperature].

Store COTEMPLA XR-ODT blister packages in the reusable travel case after removal from the carton.

17 PATIENT COUNSELING INFORMATION

Advise the patient to read the FDA-approved patient labeling (Medication Guide).

Abuse, Misuse, and Addiction

Educate patients and their families about the risks of abuse, misuse, and addiction of COTEMPLA XR-ODT, which can lead to overdose and death, and proper disposal of any unused drug [see Warnings and Precautions (5.1), Drug Abuse and Dependence (9.2), Overdosage (10)]. Advise patients to store COTEMPLA XR-ODT in a safe place, preferably locked, and instruct patients to not give COTEMPLA XR-ODT to anyone else.

Instructions for Taking COTEMPLA XR-ODT

Instruct patients and their caregivers on the following:

- The tablet should remain in the blister pack until the patient is ready to take it.
- The tablet should be taken immediately after opening the blister pack. It should not be stored for future use.
- The patient or caregiver should use dry hands when opening the blister pack.
- The patient or caregiver should remove the tablet by peeling back the foil on the blister pack. The tablet should not be pushed through the foil.
- As soon as the blister is opened, the tablet should be removed and placed on the patient's tongue.
- The whole tablet should be placed on the tongue and allowed to disintegrate without chewing or crushing.
- The tablet will disintegrate in saliva and can be swallowed. No liquid is needed to take the tablet.

Risks to Patients with Serious Cardiac Disease

Advise patients that there are potential risks to patients with serious cardiac disease, including sudden death with COTEMPLA XR-ODT use. Instruct patients to contact a healthcare provider immediately if they develop symptoms such as exertional chest pain, unexplained syncope, or other symptoms suggestive of cardiac disease [see Warnings and Precautions (5.2)] .

Increased Blood Pressure and Heart Rate

Advise patients and their caregivers that COTEMPLA XR-ODT can elevate blood pressure and heart rate [see Warnings and Precautions (5.3)] .

Psychiatric Adverse Reactions

Advise patients and their caregivers that COTEMPLA XR-ODT, at recommended doses, can cause psychotic or manic symptoms, even in patients without a prior history or psychotic symptoms or mania [see Warnings and Precautions (5.4)] .

Priapism

Advise patients, caregivers, and family members of the possibility of painful or prolonged penile erections (priapism). Instruct the patient to seek immediate medical attention in the event of priapism [see Warnings and Precautions (5.5)] .

Circulation Problems in Fingers and Toes [Peripheral vasculopathy, including Raynaud's phenomenon]

- Instruct patients about the risk of peripheral vasculopathy, including Raynaud's phenomenon, and associated signs and symptoms: fingers or toes may feel numb, cool, painful, and/or may change color from pale, to blue, to red.
- Instruct patients to report to their physician any new numbness, pain, skin color change, or sensitivity to temperature in fingers or toes.
- Instruct patients to call their physician immediately with any signs of unexplained wounds appearing on fingers or toes while taking COTEMPLA XR-ODT.
- Further clinical evaluation (e.g., rheumatology referral) may be appropriate for certain patients [see Warnings and Precautions (5.6)] .

Long-Term Suppression of Growth in Pediatric Patients

Advise patients, families, and caregivers that COTEMPLA XR-ODT can cause slowing of growth and weight loss [see Warnings and Precautions (5.7)] .

Increased Intraocular Pressure (IOP) and Glaucoma
Advise patients that IOP and glaucoma may occur during treatment with COTEMPLA XR-ODT [see Warnings and Precautions (5.9)].

Motor and Verbal Tics, and Worsening of Tourette’s Syndrome
Advise patients that motor and verbal tics and worsening of Tourette’s Syndrome may occur during treatment with COTEMPLA XR-ODT. Instruct patients to notify their healthcare provider if emergence of new tics or worsening of tics or Tourette’s syndrome occurs [see Warnings and Precautions (10)].

Alcohol Effect
Advise patients to avoid alcohol while taking COTEMPLA XR-ODT. Consumption of alcohol while taking COTEMPLA XR-ODT may result in a more rapid release of the dose of methylphenidate [see Clinical Pharmacology (12.3)].

Pregnancy Registry
Advise patients that there is a pregnancy exposure registry that monitors pregnancy outcomes in females exposed to COTEMPLA XR-ODT during pregnancy [see Use in Specific Populations (8.1)].

Medication Guide
COTEMPLA XR-ODT (koh-TEM-pluh - oh dee tee)
(methylphenidate)
extended-release orally disintegrating tablets, CII

What is the most important information I should know about COTEMPLA XR-ODT?

COTEMPLA XR-ODT may cause serious side effects, including:

- Abuse, misuse, and addiction. COTEMPLA XR-ODT has a high chance for abuse and misuse and may lead to substance use problems, including addiction. Misuse and abuse of COTEMPLA XR-ODT, other methylphenidate containing medicines, and amphetamine containing medicines, can lead to overdose and death. The risk of overdose and death is increased with higher doses of COTEMPLA XR-ODT or when it is used in ways that are not approved, such as snorting or injection

- Your healthcare provider should check your child’s risk for abuse, misuse, and addiction before treatment with COTEMPLA XR-ODT and will monitor your child during treatment.

- COTEMPLA XR-ODT may lead to physical dependence after prolonged use, even if taken as directed by your healthcare provider.

- Do not give COTEMPLA XR-ODT to anyone else. See “ What is COTEMPLA XR-ODT?” for more information.

Keep COTEMPLA XR-ODT in a safe place and properly dispose of any used medicine. See “ How should I store COTEMPLA XR-ODT?” for more information.

Tell your healthcare provider if your child has ever abused or been dependent on alcohol, prescription medicines, or street drugs.

- Risks for people with serious heart disease. Sudden death has happened in people who have heart defects or other serious heart disease.

Your healthcare provider should check your child carefully for heart problems before starting COTEMPLA XR-ODT. Tell your healthcare provider if your child has any heart problems, heart disease, or heart defects.

Call your healthcare provider or go to the nearest hospital emergency room right away if your child has any signs of heart problems such as chest pain, shortness of breath, or fainting during treatment with COTEMPLA XR-ODT.

- Increased blood pressure and heart rate.

Your healthcare provider should check your child's blood pressure and heart rate regulary during treatment with COTEMPLA XR-ODT.

- Mental (psychiatric) problems, including:
- new or worse behavior and thought problems
- new or worse bipolar illness
- new psychotic symptoms (such as hearing voices, or seeing or believing things that are not real) or new manic symptoms

Tell your healthcare provider about any mental problems your child has, or about a family history of suicide, bipolar illness, or depression.
Call your healthcare provider right away if your child has any new or worsening mental symptoms or problems during treatment with COTEMPLA XR-ODT, especially hearing voices, seeing or believing things that are not real, or new manic symptoms.

What is COTEMPLA XR-ODT?

COTEMPLA XR-ODT is a central nervous system (CNS) stimulant prescription medicine used for the treatment of Attention Deficit Hyperactivity Disorder (ADHD) in children 6 to 17 years of age. COTEMPLA XR-ODT may help increase attention and decrease impulsiveness and hyperactivity in children 6 to 17 years of age with ADHD.

COTEMPLA XR-ODT is not recommended for use in children under 6 years of age with ADHD.

COTEMPLA XR-ODT is a federally controlled substance (CII) because it contains methylphenidate that can be a target for people who abuse prescription medicines or street drugs. Keep COTEMPLA XR-ODT in a safe place to protect it from theft. Never give your COTEMPLA XR-ODT to anyone else, because it may cause death or harm them. Selling or giving away COTEMPLA XR-ODT may harm others and is against the law.

Do not give COTEMPLA XR-ODT to your child if they are:

- allergic to methylphenidate or any of the ingredients in COTEMPLA XR-ODT. See the end of this Medication Guide for a complete list of ingredients in COTEMPLA XR-ODT.
- taking, or has taken within the past 14 days, a medicine used to treat depression called a monoamine oxidase inhibitor (MAOI).

Before taking COTEMPLA XR-ODT tell your child's healthcare provider about all medical conditions, including if your child:

- has heart problems, heart desease, heart defects, or high blood pressure
- has mental problems including psychosis, mania, bipolar illness, or depression
- has circulation problems in fingers and toes
- have eye problems, including increased pressure in your eye, glaucoma, or problems with your close-up vision (farsightedness)
- have or had repeated movements or sounds (tics) or Tourette's syndrome, or have a family history of tics or Tourette's syndrome
- is pregnant or plans to become pregnant. It is not known if COTEMPLA XR-ODT will harm the unborn baby.
  - There is a pregnancy registry for females who are exposed to COTEMPLA XR-ODT during pregnancy. The purpose of the registry is to collect information about the health of females exposed to COTEMPLA XR-ODT and their baby. If your child becomes pregnant during treatment with COTEMPLA XR-ODT, talk to your healthcare provider about registering with the National Pregnancy Registry for Psychostimulants. You can register by calling 1-866-961-2388.
- is breastfeeding or plans to breastfeed. COTEMPLA XR-ODT passes into breast milk. You and your healthcare provider should decide if your child will take COTEMPLA XR-ODT or breastfeed.

Tell your healthcare provider about all of the medicines that your child takes, including prescription and over-the-counter medicines, vitamins, and herbal supplements.

COTEMPLA XR-ODT and some medicines may interact with each other and cause serious side effects. Sometimes the doses of other medicines will need to be adjusted during treatment with COTEMPLA XR-ODT.

Your healthcare provider will decide whether COTEMPLA XR-ODT can be taken with other medicines. Especially tell your healthcare provider if your child takes:

- anti-depression medicines including MAOIs

Know the medicines that your child takes. Keep a list of the medicines with you to show your healthcare provider and pharmacist. Do not start any new medicine during treatment with COTEMPLA XR-ODT without talking to your healthcare provider first.

How should COTEMPLA XR-ODT be taken?

- Take COTEMPLA XR-ODT exactly as prescribed by your healthcare provider.
- Your healthcare provider may change the dose if needed.
- Take COTEMPLA XR-ODT 1 time each day in the morning.
- COTEMPLA XR-ODT can be taken with or without food but take it the same way each time.

Take COTEMPLA XR-ODT as follows:

- Keep COTEMPLA XR-ODT in the blister pack until your child is ready to take it. Take COTEMPLA XR-ODT right after opening the blister pack. Do not store the tablet for future use.
- Use dry hands when opening the blister pack.
- Remove the tablet by peeling back the foil on the blister pack. Do not push the tablet through the foil.
- As soon as the blister is opened, remove the tablet and place it on the tongue. Do not chew or crush the tablet.
- The tablet will dissolve and can be swallowed with saliva. No liquid is needed to take the tablet.

If your child takes too much COTEMPLA XR-ODT, call your healthcare provider or Poison Help Line at 1-800-222-1222 or go to the nearest hospital emergency room right away.

What should I avoid during treatment with COTEMPLA XR-ODT?

You should avoid drinking alcohol during treatment with COTEMPLA XR-ODT.

What are possible side effects of COTEMPLA XR-ODT?

COTEMPLA XR-ODT may cause serious side effects, including:

- See "What is the most important information I should know about COTEMPLA XR-ODT?"
- Painful and prolonged erections (priapism). Priapism has happened in males who take products that contain methylphenidate. If your child develops priapism, get medical help right away.
- Circulation problems in fingers and toes (peripheral vasculopathy, including Raynaud's phenomenon). Signs and symptoms may include: Tell your healthcare provider if your child has numbness, pain, skin color change, or sensitivity to temperature in their fingers or toes.
  Call your healthcare provider right away if your child has any signs of unexplained wounds appearing on fingers or toes during treatment with COTEMPLA XR-ODT.
  - fingers or toes may feel numb, cool, painful
  - fingers or toes may change color from pale, to blue, to red
- Slowing of growth (height and weight) in children. Children should have their height and weight checked often during treatment with COTEMPLA XR-ODT. COTEMPLA XR-ODT treatment may be stopped if your child is not gaining weight or height.
- Eye problems (increased pressure in the eye and glaucoma). Call your healthcare provider right away if you or your child develop changes in your vision or eye pain, swelling, or redness.
- New or worsening tics or worsening Tourette’s syndrome. Tell your healthcare provider if you or your child get any new or worsening tics or worsening Tourette’s syndrome during treatment with COTEMPLA XR-ODT.

The most common side effects of methylphenidate products include:

- decreased appetite
- trouble sleeping
- nausea
- vomiting
- indigestion
- stomach pain
- weight loss

- anxiety
- dizziness
- irritability
- mood swings
- increased heart rate
- increased blood pressure

These are not all the possible side effects of COTEMPLA XR-ODT.

Call your doctor for medical advice about side effects. You may report side effects to FDA at 1-800-FDA-1088.

How should I store COTEMPLA XR-ODT?

- Store COTEMPLA XR-ODT at room temperature between 68°F to 77°F (20°C to 25°C).
- Store COTEMPLA XR-ODT in a safe place, like a locked cabinet.
- Store COTEMPLA XR-ODT in the blister packaging until it is ready to be taken.
- Dispose of remaining, unused, or expired COTEMPLA XR-ODT by a medicine take-back program at a U.S. Drug Enforcement Administration (DEA) authorized collection. If no take-back program or DEA authorized collector is available, mix COTEMPLA XR-ODT with an undesirable, nontoxic substance such as dirt, cat litter, or used coffee grounds to make it less appealing to children and pets. Place the mixture in a container such as a sealed plastic bag and throw away COTEMPLA XR-ODT in the household trash. Visit www.fda.gov/drugdisposal for additional information on disposal of unused medicines.

Keep COTEMPLA XR-ODT and all medicines out of the reach of children.

General information about the safe and effective use of COTEMPLA XR-ODT

Medicines are sometimes prescribed for purposes other than those listed in the Medication Guide. Do not use COTEMPLA XR-ODT for a condition for which it was not prescribed. Do not give COTEMPLA XR-ODT to other people, even if they have the same condition. It may harm them and it is against the law. You can ask your healthcare provider or pharmacist for information about COTEMPLA XR-ODT that is written for healthcare professionals.

What are the ingredients in COTEMPLA XR-ODT?

Active Ingredient: Methylphenidate

Inactive Ingredients: Mannitol, Fructose, Microcrystalline Cellulose, Crospovidone, Methacrylic Acid, Polystyrene Sulfonate, Citric Acid, Colloidal Silicon Dioxide, Grape Flavor, Natural Masking Type Powder, Triethyl Citrate, Magnesium Stearate, Ethylcellulose, Sucralose, Lake Blend Purple, and Polyethylene Glycol 3350

Manufactured for Neos Therapeutics Brands, LLC, Denver, CO 80237

For more information go to https://linkprotect.cudasvc.com/url?a=http%3a%2f%2fwww.COTEMPLAXRODT.com&c=E,1,uJnpRo76RJYGQDo8GMW8zCnFW9Wn0k16nND89VJMYg7anbFT-Thnek2P1Uts7soE5kxS-99rv0KJLMK4Fi0tUhQLe2IT7HZHVjJZmOQANFuP3n-FX1c,&typo=1 or call 1-888-319-1789

COTEMPLA XR-ODT is registered in the US Patent and Trademark Office © 2014 Neos Therapeutics, Inc.

This Medication Guide has been approved by the U.S. Food and Drug Administration

Revised: 09/2025

PRINCIPAL DISPLAY PANEL - 8.6 mg Tablet Blister Pack Carton

Contains:
NDC 70165-100-30

30 Tablets (5 x 6-count blister cards)
Travel Case

Rx Only

Cotempla XR-ODT™CII
Methylphenidate Extended-Release
Orally Disintegrating Tablets

Do not crush or chew tablets

Each tablet contains 8.6 mg of methylphenidate
(equivalent to that in a 10 mg strength
methylphenidate hydrochloride product)

8.6
mg

NEOS™
Therapeutics
PHARMACIST: Dispense the enclosed Medication Guide to each patient.

PRINCIPAL DISPLAY PANEL - 17.3 mg Tablet Blister Pack Carton

Contains:
NDC 70165-200-30

30 Tablets (5 x 6-count blister cards)
Travel Case

Rx Only

Cotempla XR-ODT™CII
Methylphenidate Extended-Release
Orally Disintegrating Tablets

Do not crush or chew tablets

Each tablet contains 17.3 mg of methylphenidate
(equivalent to that in a 20 mg strength
methylphenidate hydrochloride product)

17.3
mg

NEOS™
Therapeutics
PHARMACIST: Dispense the enclosed Medication Guide to each patient.

PRINCIPAL DISPLAY PANEL - 25.9 mg Tablet Blister Pack Carton

Contains:
NDC 70165-300-30

30 Tablets (5 x 6-count blister cards)
Travel Case

Rx Only

Cotempla XR-ODT™CII
Methylphenidate Extended-Release
Orally Disintegrating Tablets

Do not crush or chew tablets

Each tablet contains 25.9 mg of methylphenidate

(equivalent to that in a 30 mg strength
methylphenidate hydrochloride product)

25.9
mg

NEOS™
Therapeutics
PHARMACIST: Dispense the enclosed Medication Guide to each patient.